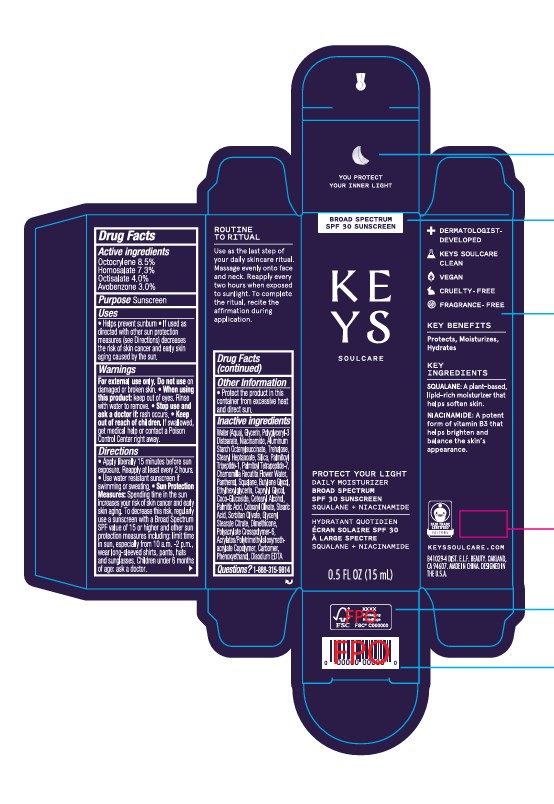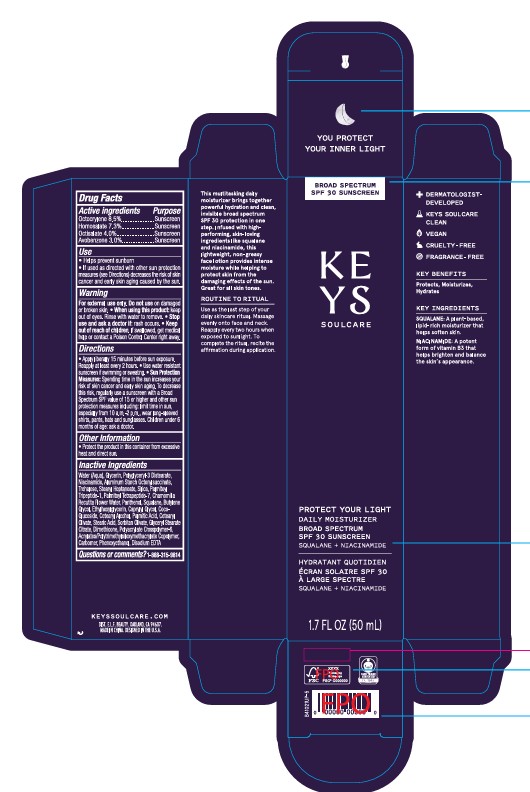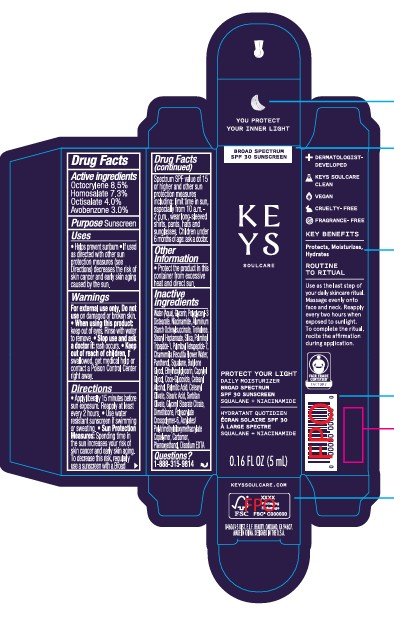 DRUG LABEL: KEYS SOULCARE DAILY MOISTURIZER BROAD SPECTRUM SPF30 SUNSCREEN
NDC: 76354-454 | Form: CREAM
Manufacturer: e.l.f. Cosmetics, Inc
Category: otc | Type: HUMAN OTC DRUG LABEL
Date: 20250217

ACTIVE INGREDIENTS: AVOBENZONE 30 mg/1 mL; HOMOSALATE 73 mg/1 mL; OCTISALATE 40 mg/1 mL; OCTOCRYLENE 85 mg/1 mL
INACTIVE INGREDIENTS: HYDROXYETHYL ACRYLATE/SODIUM ACRYLOYLDIMETHYL TAURATE COPOLYMER (45000 MPA.S AT 1%); POLYACRYLATE CROSSPOLYMER-6; WATER; GLYCERIN; POLYGLYCERYL-3 DISTEARATE; NIACINAMIDE; ALUMINUM STARCH OCTENYLSUCCINATE; TREHALOSE; SILICON DIOXIDE; STEARYL HEPTANOATE; PHENOXYETHANOL; PALMITOYL TRIPEPTIDE-1; PALMITOYL TETRAPEPTIDE-7; CHAMOMILE FLOWER OIL; PANTHENOL; SQUALANE; BUTYLENE GLYCOL; STEARIC ACID; PALMITIC ACID; CETEARYL OLIVATE; SORBITAN OLIVATE; CETOSTEARYL ALCOHOL; GLYCERYL STEARATE CITRATE; STEARYL CAPRYLATE; DIMETHICONE; COCO GLUCOSIDE; CARBOMER HOMOPOLYMER, UNSPECIFIED TYPE; CAPRYLYL GLYCOL; ETHYLHEXYLGLYCERIN; EDETATE DISODIUM ANHYDROUS

KEYS SOULCARE DAILY MOISTURIZER BROAD SPECTRUM SPF30 SUNSCREEN

Active ingredients

Avobenzone 3.0%

Homosalate 7.3%

Octisalate 4%

Octocrylene 8.5%

Purpose

Sunscreen

Use

- Helps prevent sunburn
- If used as directed with other sun protection measures (see Directions) decreases the risk of skin cancer and early skin aging caused by the sun.

Warning

For external use only.

Do not use

on damaged or broken skin.

When using this product:

keep out of eyes, Rinse with water to remove.

Stop use and ask a doctorif:

rash occurs.

Keep out of reach of children.

If swallowed, get medical help or conact a Poison Control Center right away.

Directions

- Apply libreally 15 minutes before sun exposure, Reapply at least every 2 hours.
- Use water resistant sunscreen if swimming or sweating.
- Spending time in the sun increases your risk of skin cancer and early skin aging. To decrease this risk, regularly use a sunscreen with a Braod Spectrum SPF value of 15 or higher and other sun protection measures including: limit time in sun, especially from 10 a.m.-2 p.m., wear long-sleeved shirts, pants, hats and sunglasses. Children under 6 months of age: ask a doctor. Sun Protection Measures:

Other Information

- Protect the product in this container from excessive heat and direct sun.

Inactive Ingredients

Water (Aqua), Glycerin, Polyglyceryl-3 Distearate, Niacinamide, Aluminum Starch Octenylsuccinate, Trehalose, Stearyl Heptanoate, Silica, Palmitoyl Tripeptide-1, Palmitoyl Tetrapeptide-7, Chamomilla Recutita Flower Water, Panthenol, Squalane, Butylene Glycol, Ethylhexylglycerin, Caprylyl Glycol, Coco-Glucoside, Cetearyl Alcohol, Palmitic Acid, Cetearyl Olivate, Stearic Acid, Sorbitan Olivate, Glyceryl Stearate Citrate, Dimethicone, Polyacrylate Crosspolymer-6, Acrylates/Polytrimethylsiloxymethacrylate Copolymer, Carbomer, Phenoxyethanol, Disodium EDTA

Questions or comments?

1-888-315-9814